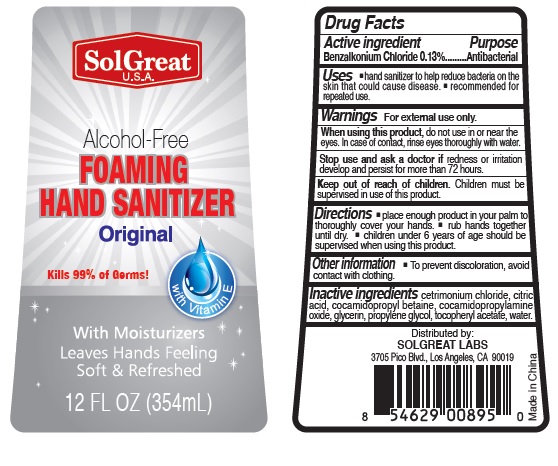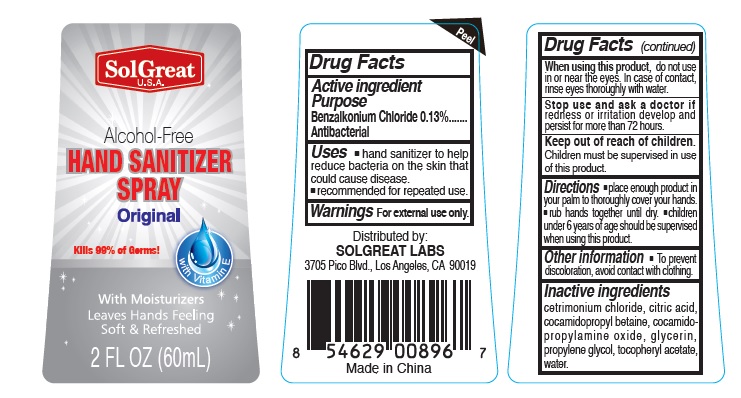 DRUG LABEL: SolGreat Alcohol-Free Foaming Hand Sanitizer
NDC: 73913-002 | Form: SPRAY
Manufacturer: PANATURAL USA, INC.
Category: otc | Type: HUMAN OTC DRUG LABEL
Date: 20200327

ACTIVE INGREDIENTS: BENZALKONIUM CHLORIDE 1.3 mg/1 mL
INACTIVE INGREDIENTS: CETRIMONIUM CHLORIDE; CITRIC ACID MONOHYDRATE; COCAMIDOPROPYL BETAINE; COCAMIDOPROPYLAMINE OXIDE; GLYCERIN; PROPYLENE GLYCOL; .ALPHA.-TOCOPHEROL ACETATE; WATER

SolGreat Alcohol-Free Hand Sanitizer

Active lngredient

Benzalkonium Chloride

Purpose

Antibacterial

Uses

- hand sanitizer to help reduce bacteria on the skin that could cause disease.
- recommended for repeated use.

Warnings

For external use only.

When using this product, do not use in or near the eyes. In case of contact, rinse eyes thoroughly with water,

Stop use and ask a doctor if redness or irritation develop and persist for more than 72 hours.

Directions

- place enough product in your palm to thoroughly cover your hands.
- rub hands together until dry.
- children under 6 years of age should be supervised when using this product.

Inactive Ingredients

cetrimonium chloride citric acid, cocamidopropyl betaine, cocamidopropylamine oxide, glycerin, propylene glycol, tocopheryl acetate, water.

Keep out of reach of children.

Children must be supervised in use of this product.

Other information

To prevent discoloration, avoid contact with clothing.